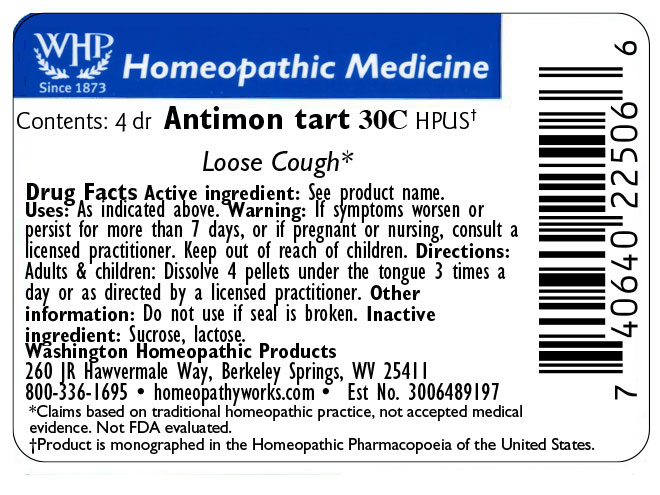 DRUG LABEL: Antimonium tartaricum
NDC: 71919-829 | Form: PELLET
Manufacturer: Washington Homeopathic Products
Category: homeopathic | Type: HUMAN OTC DRUG LABEL
Date: 20250911

ACTIVE INGREDIENTS: ANTIMONY POTASSIUM TARTRATE 30 [hp_C]/1 1
INACTIVE INGREDIENTS: SUCROSE; LACTOSE

Antimonium tartaricum

ACTIVE INGREDIENT

ANTIMONIUM TART

USES

Indicated for loose cough

KEEP OUT OF REACH OF CHILDREN

As with all medicines, keep out of reach of children.

INDICATIONS

ANTOMONIUM TART Loose cough

STOP USE AND ASK DOCTOR

If symptoms worsen or persist for more than 7 days, or if pregnant or nursing, consult a licensed practitioner.

DIRECTIONS

Directions: Adults & children: Dissolve 4 pellets under the tongue 3 times a day or as directed by a licensed practitioner. Other information: Do not use if seal is broken.

INACTIVE INGREDIENT SECTION

SUCROSE/LACTOSE

PACKAGE LABEL DISPLAY

The OTC potency range of ANTIMONIUM TART is 30C – 200C.

Availability is subject to change.